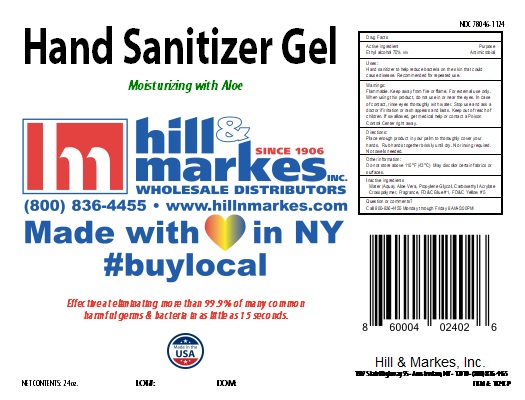 DRUG LABEL: Hand Sanitizer Gel
NDC: 78046-1124 | Form: SOLUTION
Manufacturer: Hill & Markes, Inc.
Category: otc | Type: HUMAN OTC DRUG LABEL
Date: 20200519

ACTIVE INGREDIENTS: ALCOHOL 0.7 mL/1 mL
INACTIVE INGREDIENTS: WATER; ALOE VERA LEAF; PROPYLENE GLYCOL; AMMONIUM ACRYLOYLDIMETHYLTAURATE; FD&C BLUE NO. 1; HEPTANAL; FD&C YELLOW NO. 5

DESCRIPTION

Hand Sanitizer Gel

Moisturizing with Aloe

Effective at eliminating more than 99.9% of many common harmful germs & bacteria in as little as 15 seconds.

Active Ingredient(s)

Ethyl alcohol 70% v/v Purpose Antimicrobial

Purpose

Antimicrobial

Use

Hand sanitizer to help reduce bacteria on the skin that could cause disease Recommended for repeated use.

Warnings

Flammable. Keep away from fire or flame.

For external use only

Do not use

- in children less than 2 months of age
- on open skin wounds

When using this product keep out of eyes, ears, and mouth. In case of contact with eyes, rinse eyes thoroughly with water.
Stop use and ask a doctor if irritation or rash occurs. These may be signs of a serious condition.
Keep out of reach of children. If swallowed, get medical help or contact a Poison Control Center right away.

Stop use and ask a doctor if irritation or rash occurs. These may be signs of a serious condition.

Keep out of reach of children. If swallowed, get medical help or contact a Poison Control Center right away.

Directions

Place enough product in your palm to thoroughly cover your hands Rub hands together briskly until dry

No rinsing required

No towels needed

Other information

Do not store above 110°F (43°C) May discolor certain fabrics or surfaces.

Inactive ingredients

Water (Aqua), Aloe Vera, Propylene Glycol, Carboxethyl Acrylate Crosspolymer, Fragrance, FD&C Blue #1, FD&C Yellow #5

Package Label - Principal Display Panel

709.76 mL NDC: 78046-1124-1